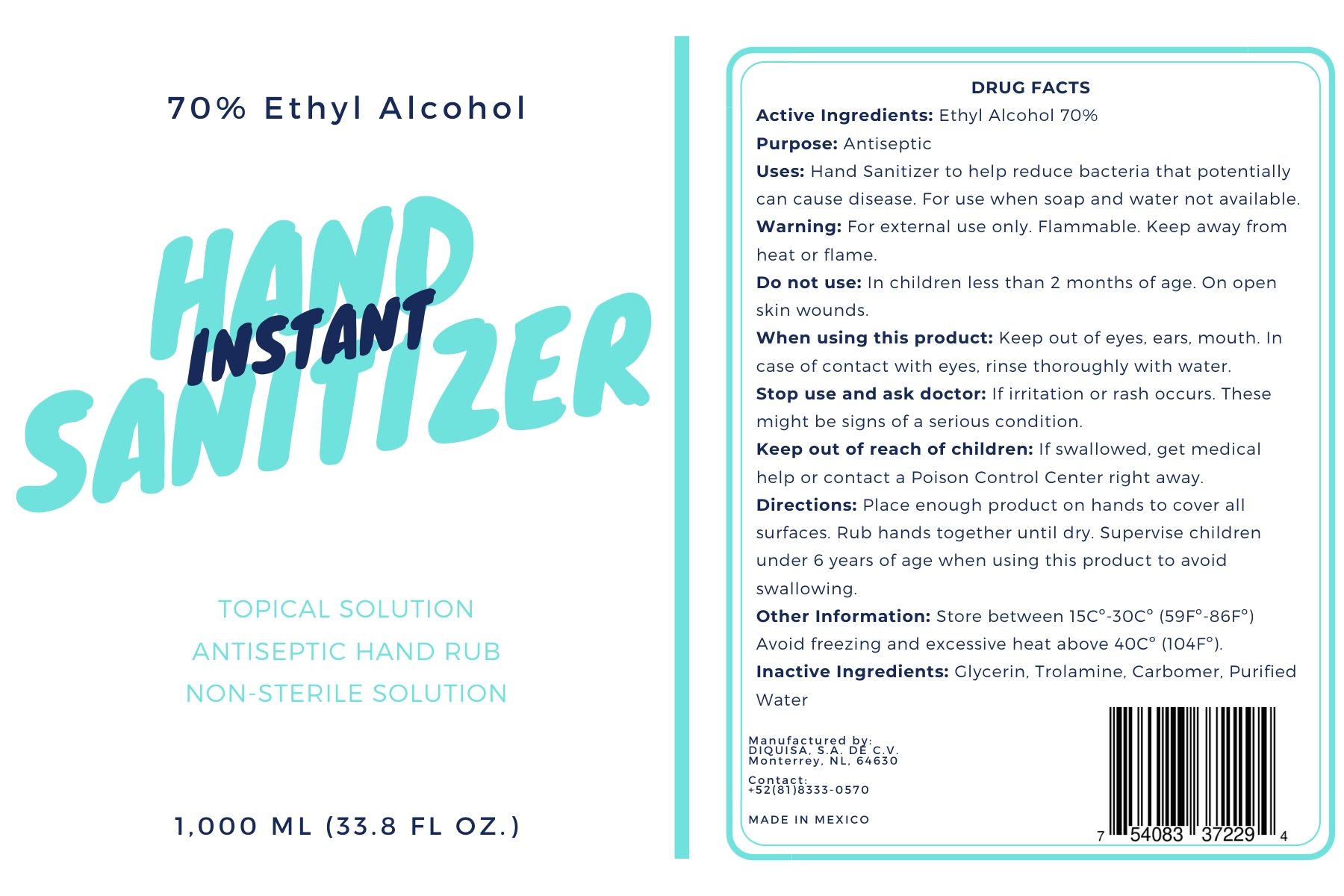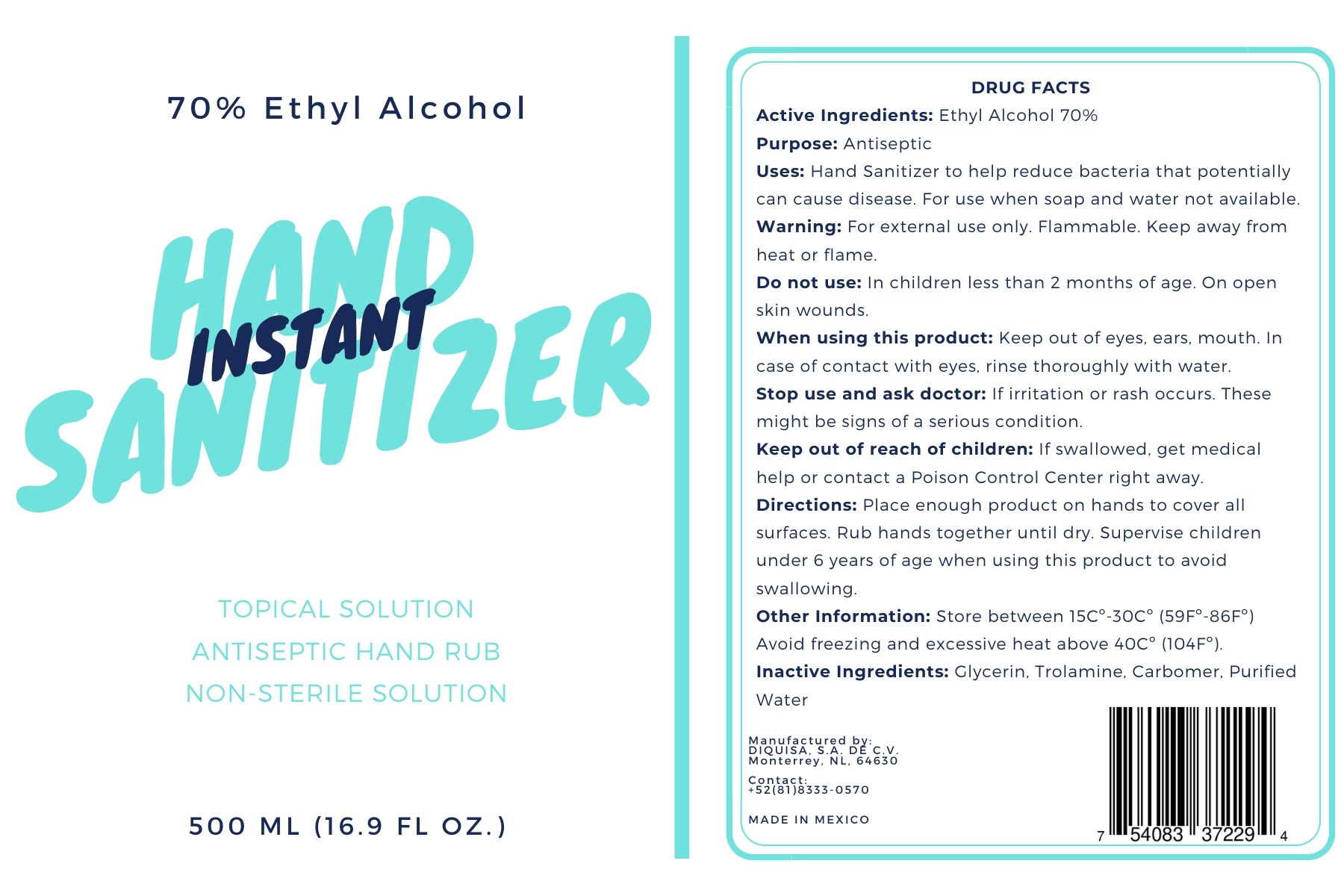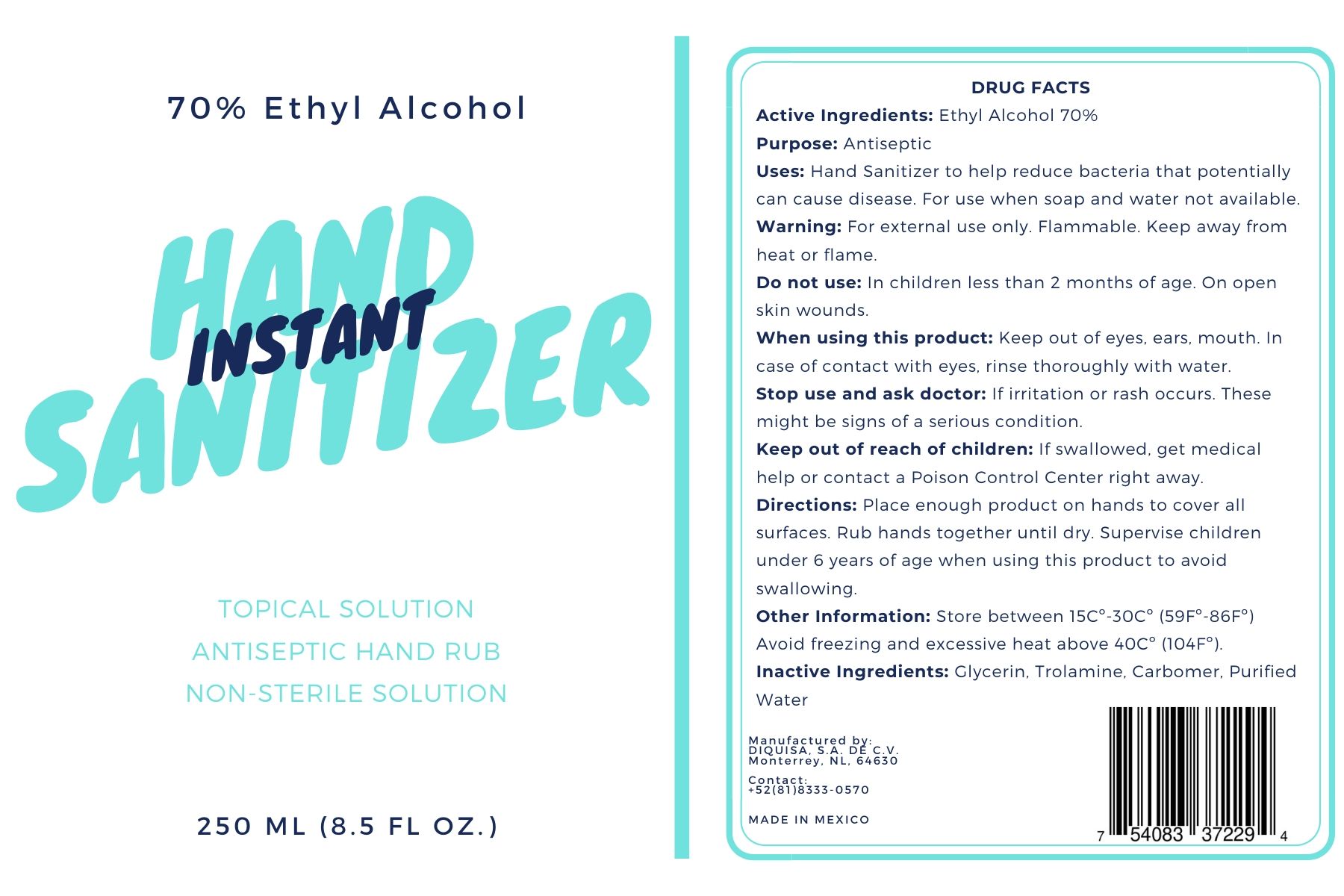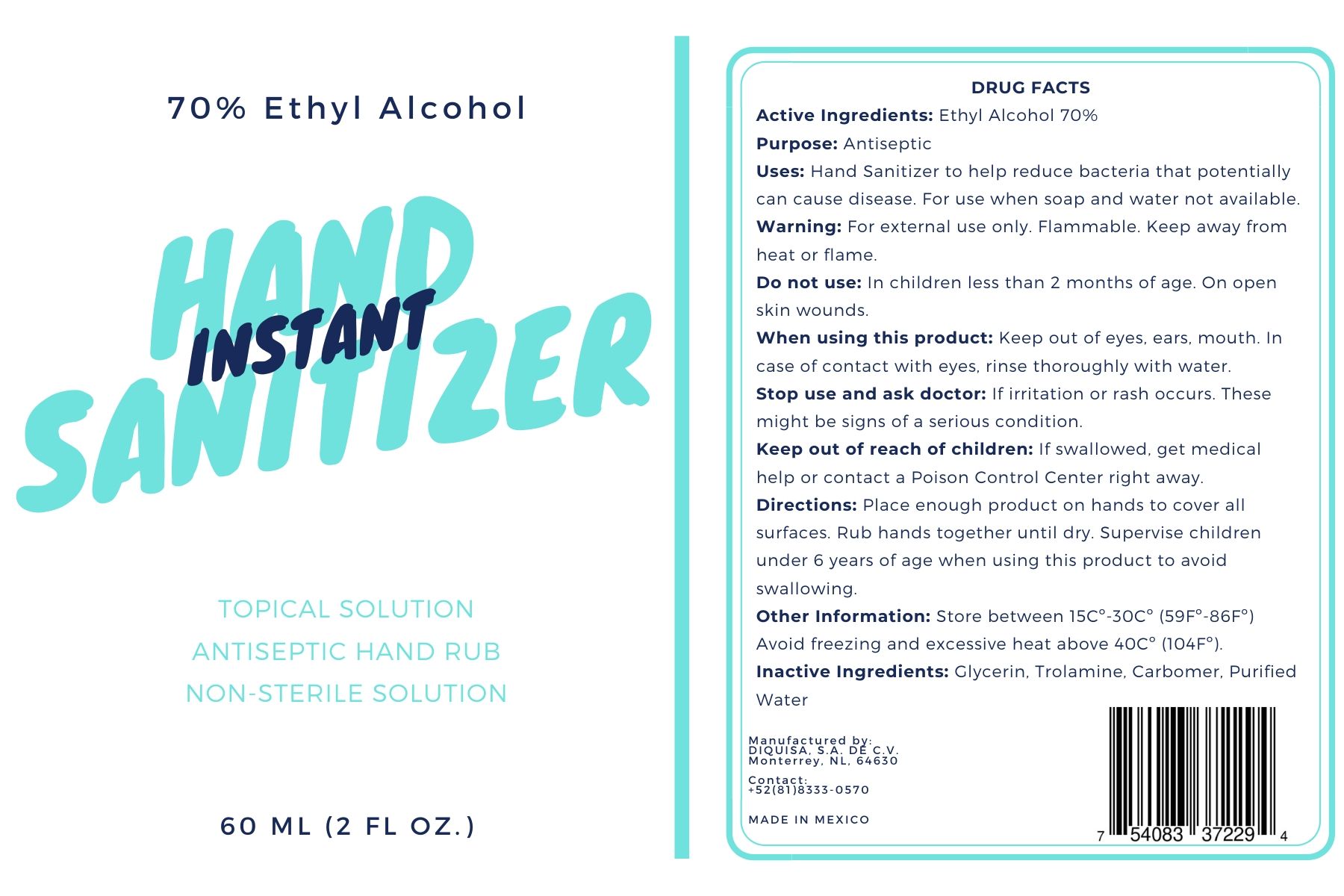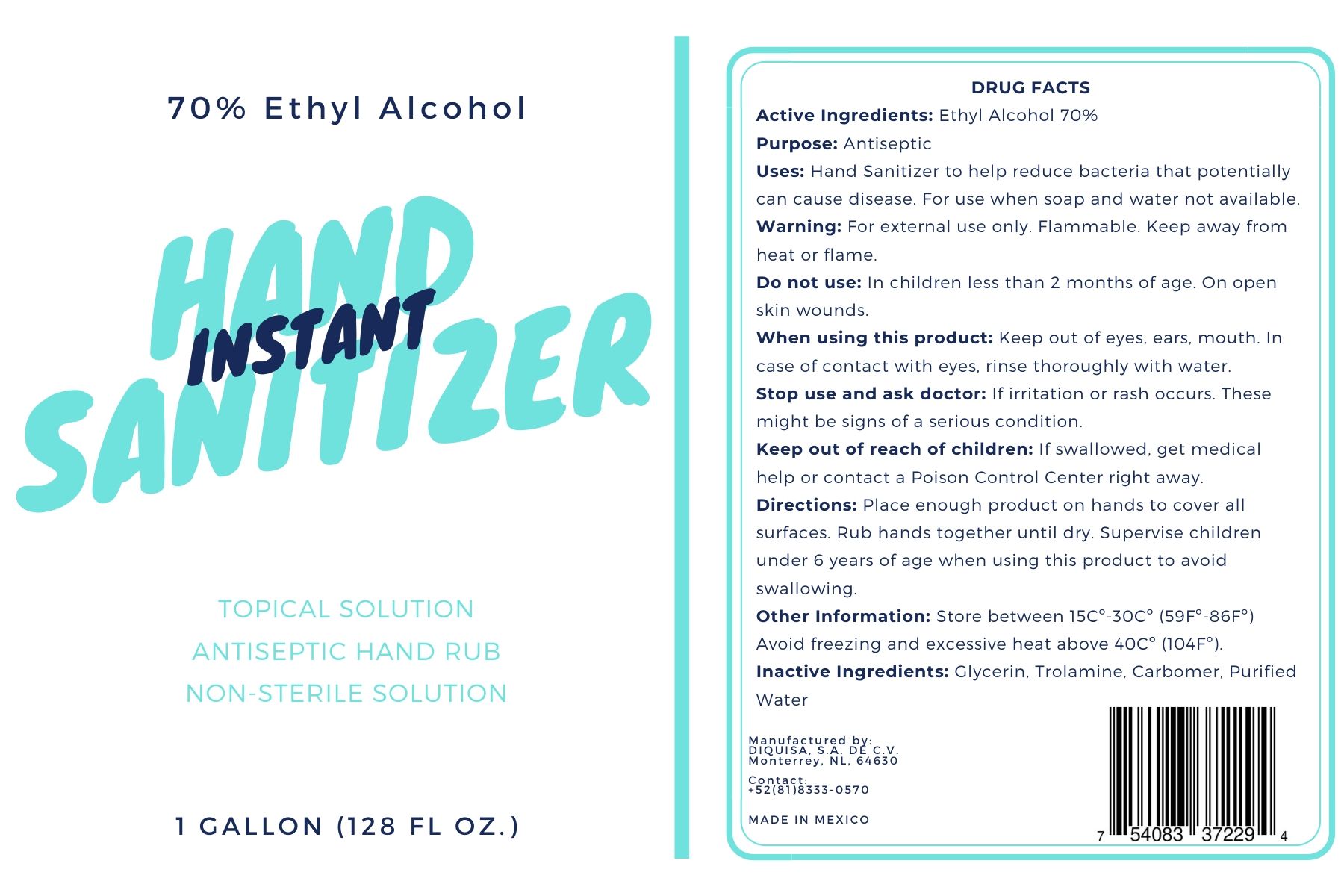 DRUG LABEL: Hand Sanitizer
NDC: 78361-002 | Form: GEL
Manufacturer: Diquisa, S.A. de C.V
Category: otc | Type: HUMAN OTC DRUG LABEL
Date: 20200605

ACTIVE INGREDIENTS: ALCOHOL 70 mL/100 mL
INACTIVE INGREDIENTS: GLYCERIN 0.3 mL/100 mL; WATER; TROLAMINE 0.1 mL/100 mL; CARBOMER HOMOPOLYMER, UNSPECIFIED TYPE 0.4 mL/100 mL

Hand Sanitizer Gel

The hand sanitizer gel is manufactured using only the following United States Pharmacopoeia (USP) grade ingredients in the preparation of the product.

1. Alcohol (ethanol) (USP or Food Chemical Codex (FCC) grade) (70%, volume/volume (v/v)) in an aqueous solution denatured according to Alcohol and Tobacco Tax and Trade Bureau regulations in 27 CFR part 20.
2. Glycerol (0.2% v/v).
3. Trolamine (0.15% v/v).
  d. Carbomer (0.3 %)
  e. Sterile distilled water or boiled cold water.

Active Ingredient(s)

Alcohol 70% v/v. Purpose: Antiseptic

Purpose

Antiseptic

Use

Hand Sanitizer to help reduce bacteria that potentially can cause disease. For use when soap and water are not available.

Warnings

For external use only. Flammable. Keep away from heat or flame

Do not use

- in children less than 2 months of age
- on open skin wounds

When using this product keep out of eyes, ears, and mouth. In case of contact with eyes, rinse eyes thoroughly with water.
Stop use and ask a doctor if irritation or rash occurs. These may be signs of a serious condition.
Keep out of reach of children. If swallowed, get medical help or contact a Poison Control Center right away.

Stop use and ask a doctor if irritation or rash occurs. These may be signs of a serious condition.

Keep out of reach of children. If swallowed, get medical help or contact a Poison Control Center right away.

Inactive ingredients

glycerin, trolamine, carbomer, streriled or distilled water

Other information

- Store between 15-30C (59-86F)
- Avoid freezing and excessive heat above 40C (104F)

Directions

- Place enough product on hands to cover all surfaces. Rub hands together until dry.
- Supervise children under 6 years of age when using this product to avoid swallowing.

Package Label - Principal Display Panel

1 gallon NDC: 78361-002-04

1000 ml NDC 78361-002-06

500 ml NDC 78361-002-07
250 ml NDC 78361-002-08
60 ml NDC 78361-002-09